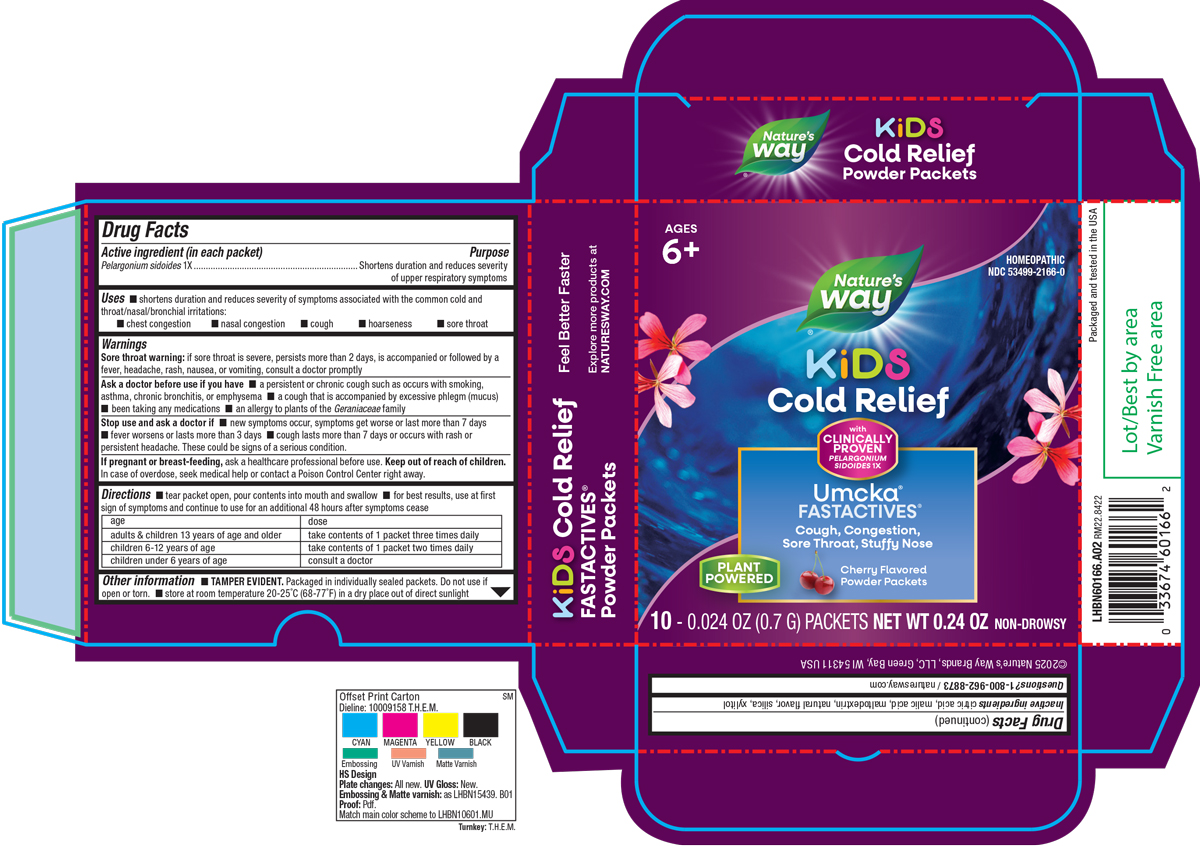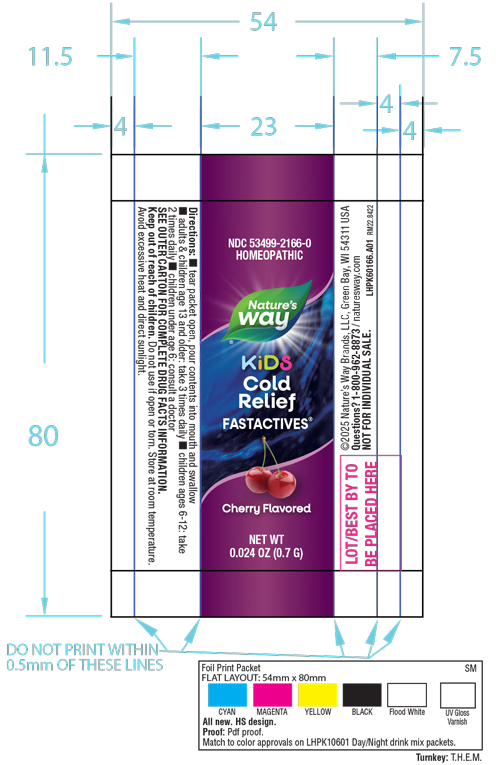 DRUG LABEL: Cold Relief Kids FastActives Cherry
NDC: 53499-2166 | Form: POWDER
Manufacturer: Schwabe North America, Inc.
Category: homeopathic | Type: HUMAN OTC DRUG LABEL
Date: 20250519

ACTIVE INGREDIENTS: PELARGONIUM SIDOIDES ROOT 1 [hp_X]/700 mg
INACTIVE INGREDIENTS: CITRIC ACID MONOHYDRATE; MALIC ACID; MALTODEXTRIN; SILICON DIOXIDE; XYLITOL

Cold Relief Kids Cherry FastActives

Active Ingredient

Pelargonium sidoides 1X

Inactive Ingredients

Citric Acid

Malic Acid

Maltodextrin

Natural Flavor

Silica

Xylitol

Dosage & Administration

Tear packet open, pour contents into mouth and swallow.

For best results, use at first sign of symptoms and continue to use for an additional 48 hours after symptoms cease.

Adults and children 13 years of age and older: take contents of 1 packet three times daily

Children 6-12 years of age: take contents of 1 packet two times daily

Children under 6 years of age: consult a doctor

Indications & Usage

Shortens duration and reduces severity of symptoms associated with the common cold and throat/nasal/bronchial irritations: chest congestion, nasal congestion, cough, hoarseness, sore throat.

Purpose

Shortens duration and reduces severity of symptoms associated with the common cold and throat/nasal/bronchial irritations: chest congestion, nasal congestion, cough, hoarseness, sore throat.

Warning

Sore throat warning: if sore throat is severe, persists more than 2 days, is accompanied or followed by a fever, headache, rash, nausea, or vomiting, consult a doctor pomptly.

Ask Doctor

Ask a doctor before use if you have a peristent or chronic cough such as occurs occurs with smoking, asthma, chronic bronchitis, or emphysema, a cough that is accompanied by excessive phlegm (mucus), been taking any medications, an allergy to plant to the Geraniaceae family.

Stop Use

Stop use and ask a doctor if new symptoms occur, symptoms get worse or last more than 7 days, fever worsens or lasts more than 3 days, cough lasts more than 7 days or occurs with rash or persistent headache.

These could be signs of a serious condition.

Pregnant or breast feeding

If you are pregnant or breast-feeding, ask a healthcare professional before use.

Keep out of reach of children

Overdose

In case of overdose, seek medical help or contract a Posion Control Center right away.